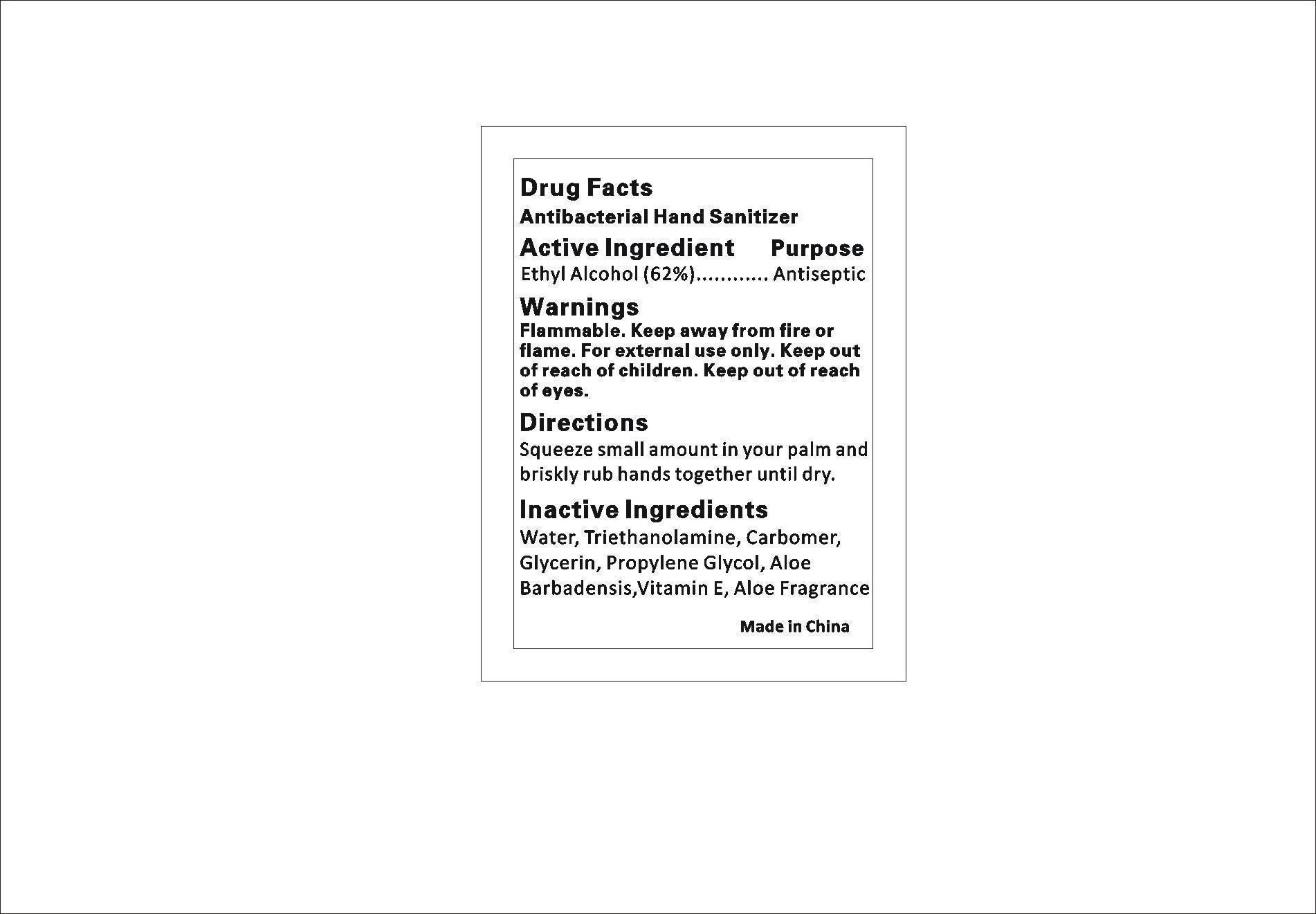 DRUG LABEL: HAND SANITIZER
NDC: 47993-200 | Form: LIQUID
Manufacturer: NINGBO JIANGBEI OCEAN STAR TRADING CO.,LTD
Category: otc | Type: HUMAN OTC DRUG LABEL
Date: 20171213

ACTIVE INGREDIENTS: ALCOHOL 62 g/100 g
INACTIVE INGREDIENTS: WATER 19.5 g/100 g; GLYCERIN 5 g/100 g; PROPYLENE GLYCOL 5 g/100 g; CARBOMER HOMOPOLYMER TYPE C 8 g/100 g; ISOPROPYL MYRISTATE 0.2 g/100 g; .ALPHA.-TOCOPHEROL ACETATE, D- 0.2 g/100 g; AMINOMETHYLPROPANOL 0.1 g/100 g

Active Ingredients

Active ingredients--------------purpose

Ethyl Alcohol 62%------------antiseptic

Uses:
Reduces bacteria on the skin. Recommended for repeated use.

Warnings:

For external use only.Flammable:Keep away from heat for flame.Do no use in or near the eyes. In case of contact, rinse eyes thoroughly with water.

Directions:

Place enough product in your palm to thoroughly cover your hands. Rub hands together briskly until dry.

Other Information

Do not store above 110F(43C) May discolor certain fabric or surfaces. Harmful to wood finishes and plastics.

KEEP OUT OF REACH OF CHILDREN

Children under 6 years of age should be super vised when using this product.

Inactive Ingredients:

Water,Glycerin,Isopropyl Myristate, Propylene Glycol,Tocopheryl Acetate, Aminomethyl Propanol, Carbomer, Fragrance